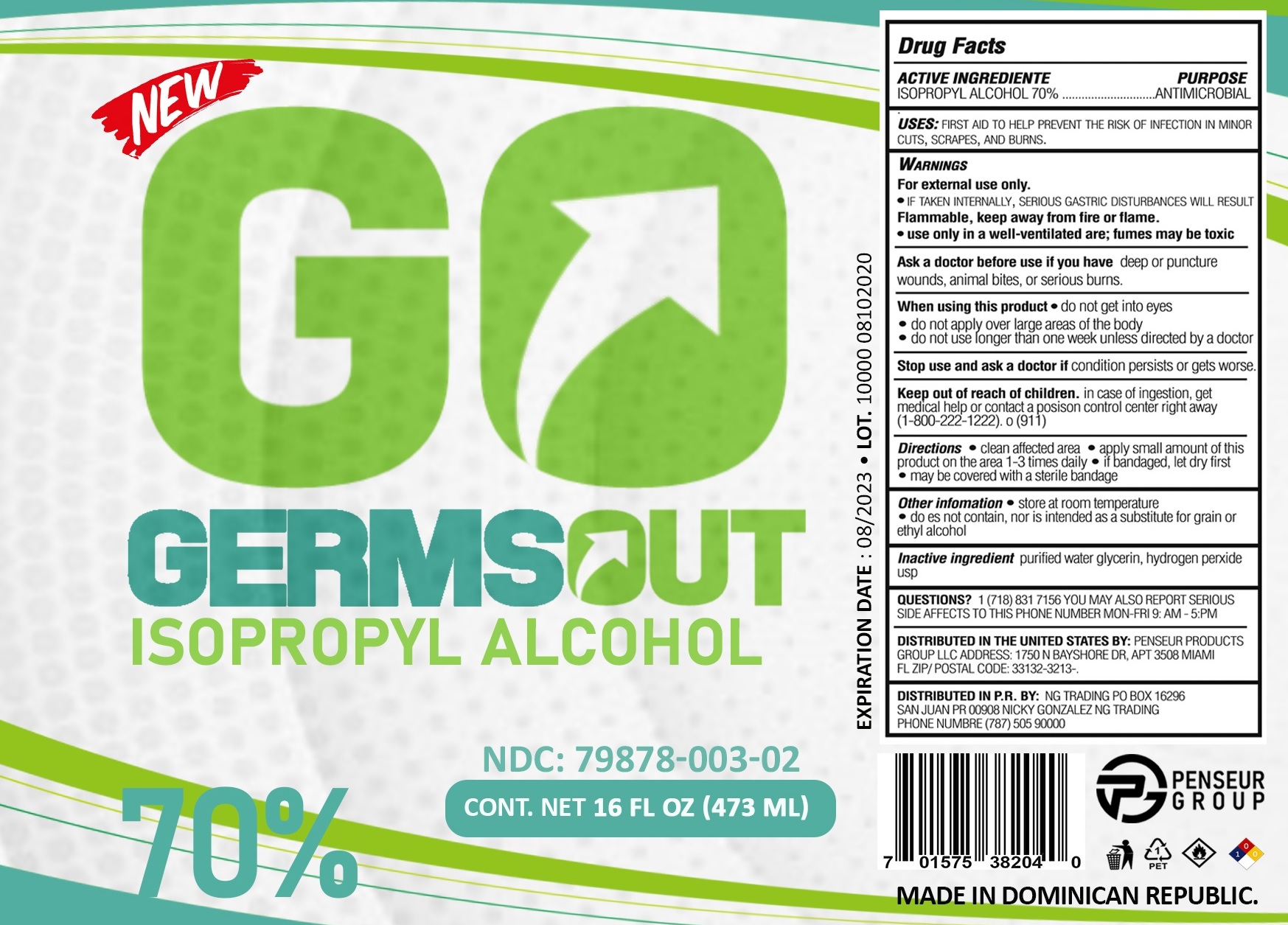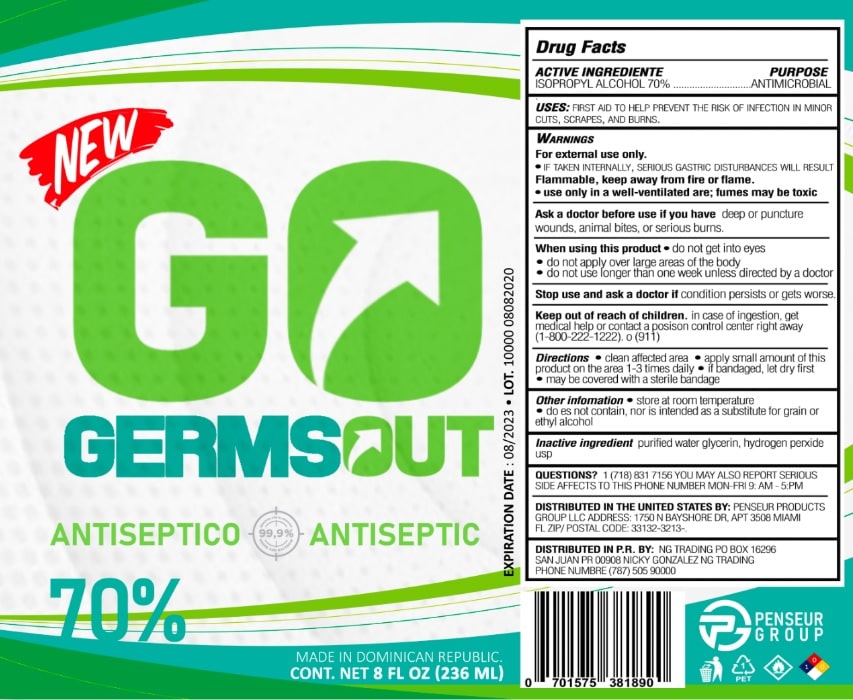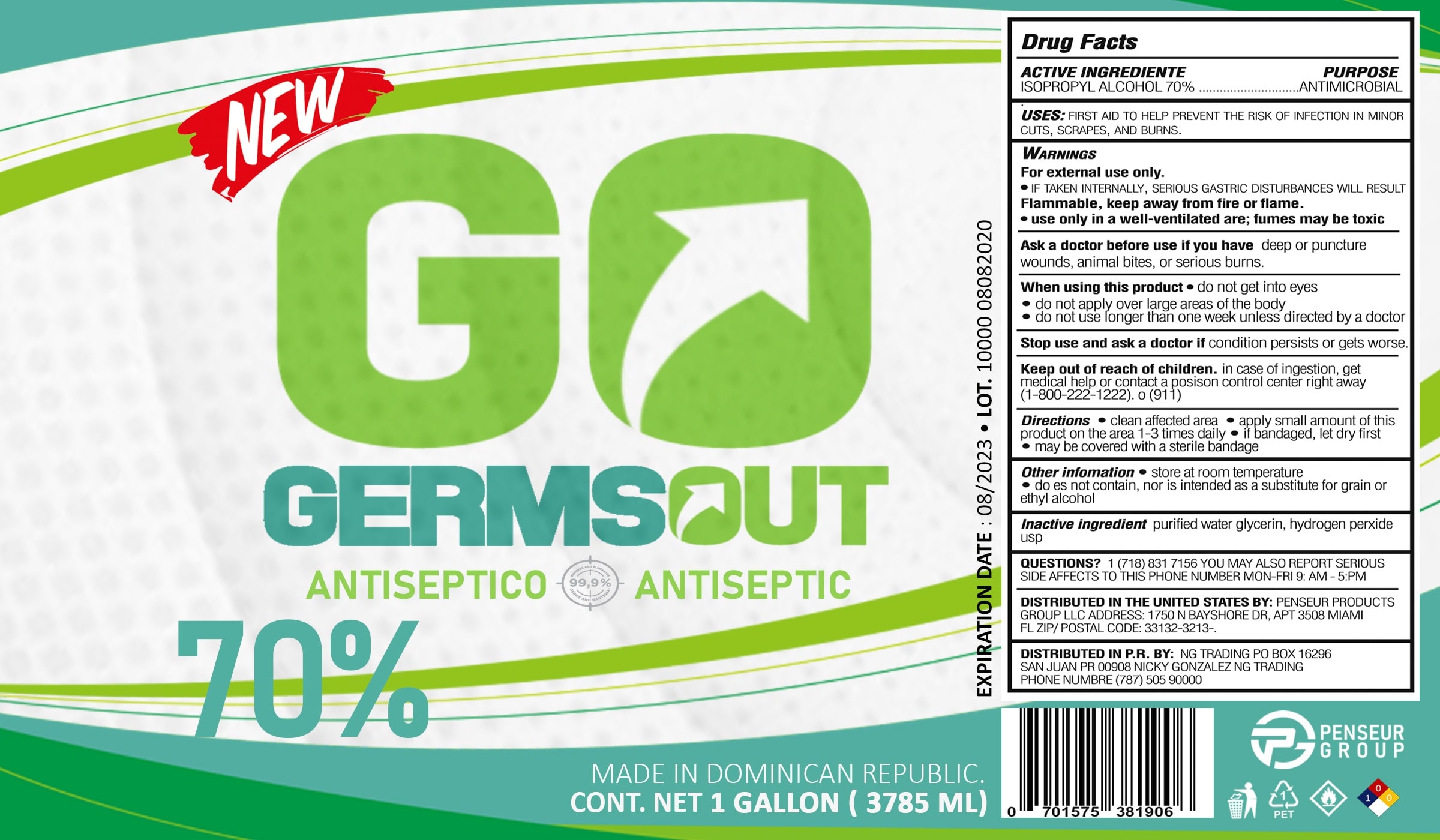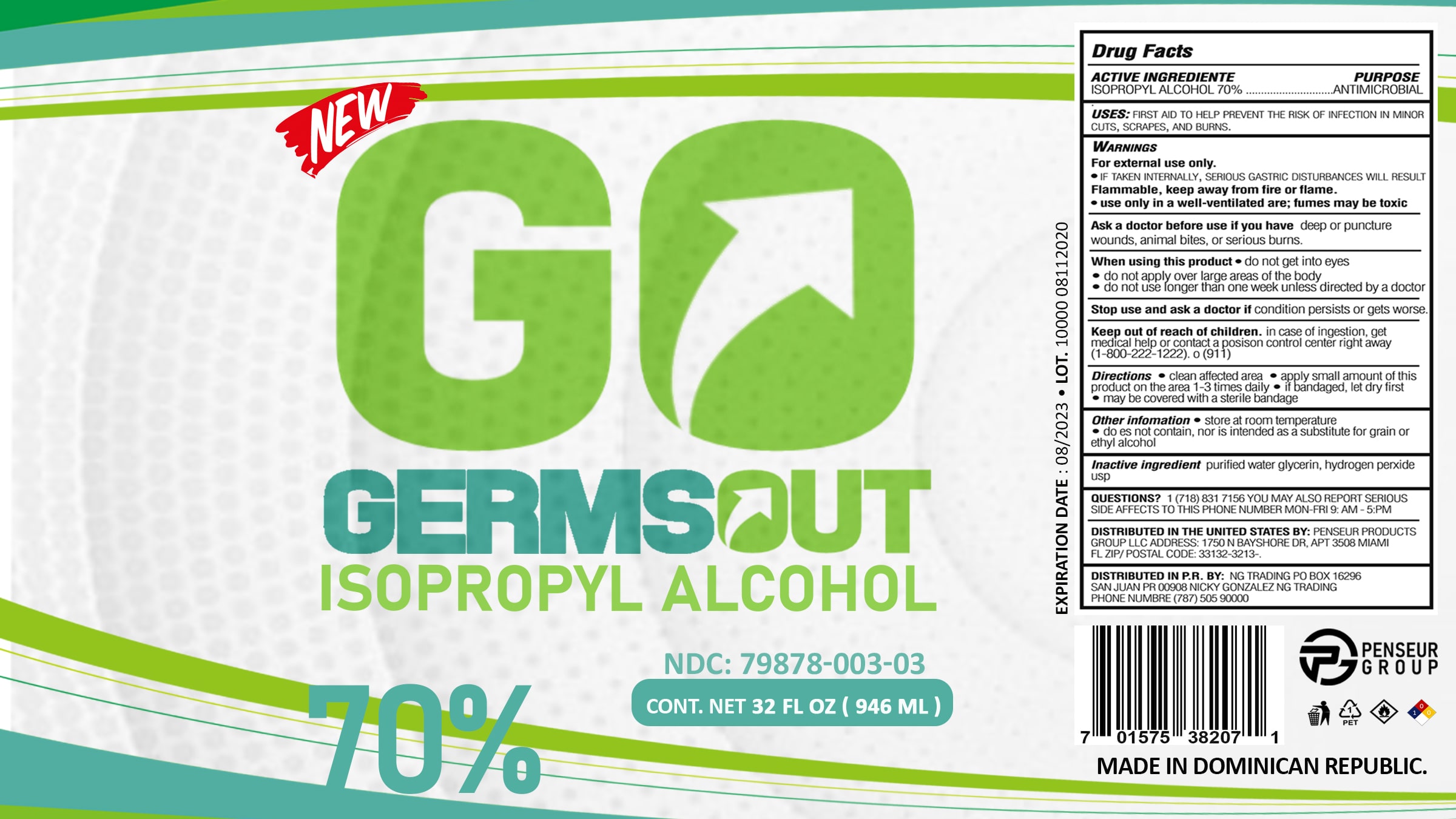 DRUG LABEL: Germs Out
NDC: 79878-003 | Form: LIQUID
Manufacturer: PENSEUR PRODUCTS GROUP LLC
Category: otc | Type: HUMAN OTC DRUG LABEL
Date: 20200915

ACTIVE INGREDIENTS: ISOPROPYL ALCOHOL 70 mL/100 mL
INACTIVE INGREDIENTS: GLYCERIN; HYDROGEN PEROXIDE; WATER

Active Ingredient(s)

Isopropyl Alcohol 70% v/v. Purpose: Antiseptic

Purpose

ANTIMICROBIAL

Use

First Aid to help prevent the risk of infection in minor cuts, scrapes, and burns.

Warnings

For external use only.

If taken internally, serious gastric disturbances will result.

Flammable. Keep away from fire or flame

use only in a well-ventilated area; fumes may be toxic.

Do not use

Ask a doctor before use if you have deep or puncture wounds, animal bites, or serious burns.

When using this product do not get into eyes.

Do not apply over large areas of the body.

Do not use longer than one week unless directed by a doctor.

Stop use and ask a doctor if condition persists or gets worse.
Keep out of reach of children. In case of infestion get medical help or contact a Poison Control Center right away (1-800-222-1222) or 911.

Stop use and ask a doctor if irritation or rash occurs. These may be signs of a serious condition.

Keep out of reach of children. If swallowed, get medical help or contact a Poison Control Center right away.

Directions

- Clean affected area.
- Apply small amount of this product on the area 1-3 times daily.
- if bandaged, let dry first.
- may be covered with a sterile bandage.

Other information

- Store between 15-30C (59-86F)
- Avoid freezing and excessive heat above 40C (104F)

Inactive ingredients

glycerin, hydrogen peroxide, purified water USP

Package Label - Principal Display Panel

236 ml NDC: 79878-003-00

3785 ml NDC: 79878-003-01

473 ml NDC: 79878-003-02

946 ml NDC: 79878-003-03